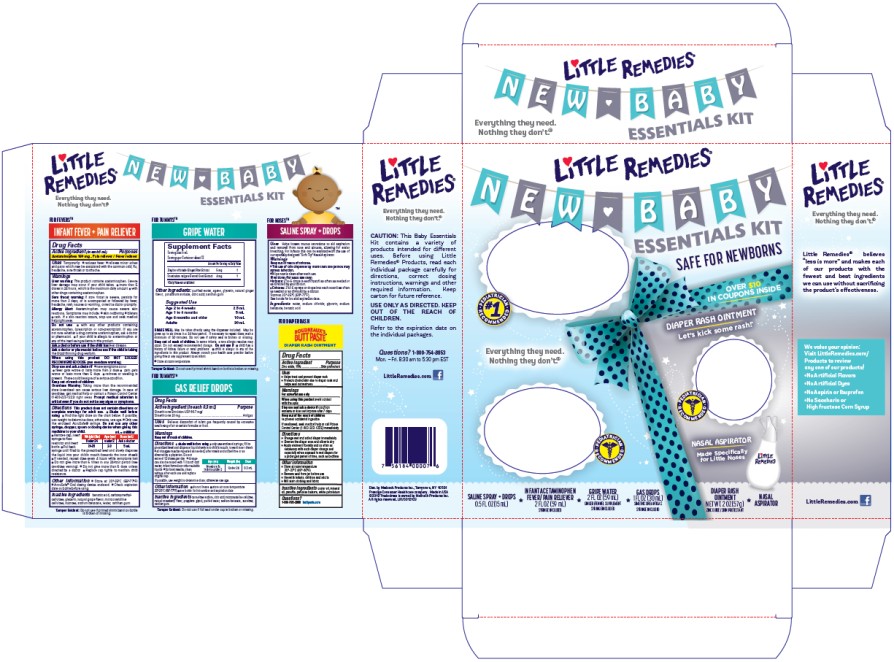 DRUG LABEL: LITTLE REMEDIES NEW BABY ESSENTIALS
NDC: 63029-615 | Form: KIT | Route: ORAL
Manufacturer: Medtech Products Inc.
Category: otc | Type: HUMAN OTC DRUG LABEL
Date: 20241206

ACTIVE INGREDIENTS: ACETAMINOPHEN 160 mg/5 mL; DIMETHICONE 20 mg/0.3 mL; ZINC OXIDE 16 g/113 g; GINGER 5 mg/5 mL; FENNEL 4 mg/5 mL
INACTIVE INGREDIENTS: BENZOIC ACID; CARBOXYMETHYLCELLULOSE; GLYCERIN; MICROCRYSTALLINE CELLULOSE; SUCROSE; SODIUM BENZOATE; WATER; XANTHAN GUM; CARBOXYMETHYLCELLULOSE SODIUM; CITRIC ACID MONOHYDRATE; MICROCRYSTALLINE CELLULOSE; PROPYLENE GLYCOL; WATER; SODIUM BENZOATE; SUCRALOSE; XANTHAN GUM; CASTOR OIL; MINERAL OIL; PARAFFIN; BALSAM PERU; PETROLATUM; WATER; AGAVE TEQUILANA JUICE; GLYCERIN; CITRIC ACID MONOHYDRATE; POTASSIUM SORBATE; XANTHAN GUM

Little Remedies New Baby Essentials Kit

FOR FEVERSTM

INFANT FEVER + PAIN RELIEVER Acetaminophen

Drug Facts

Active ingredient

(in each 5 mL)

Acetaminophen 160 mg

Purpose

Pain reliever / Fever reducer

Uses

Temporarily:

- reduces fever
- relieves minor aches and pains which may be associated with the common cold, flu, headache, sore throat or toothache.

Warnings

Liver warning: This product contains acetaminophen. Severe liver damage may occur if your child takes ▪ more than 5 doses in 24 hours, which is the maximum daily amount ▪ with other drugs containing acetaminophen.

Sore Throat Warning: If sore throat is severe, persists for more than 2 days, or is accompanied or followed by fever, headache, rash, nausea or vomiting, consult a doctor promptly.

Allergy Alert: Acetaminophen may cause severe skin reactions. Symptoms may include: ▪ skin reddening ▪ blisters ▪ rash. If a skin reaction occurs, stop use and seek medical help right away.

Do not use

- with any other products containing acetaminophen (prescription or non-prescription).

If you are not sure whether a drug contains acetaminophen, ask a doctor or pharmacist.

- if your child is allergic to acetaminophen or any of the inactive ingredients in this product.

Ask a doctor before use if the child has

liver disease.

Ask a doctor or pharmacist before use if the child is

taking the blood thinning drug warfarin.

When using this product

do not exceed recommended dose (see overdose warning)

Stop use and ask a doctor if

- new symptoms occur
- fever gets worse or lasts more than 3 days
- pain gets worse or lasts more than 5 days
- redness or swelling is present. These could be signs of a serious condition.

Keep out of reach of children.

Overdose Warning: Taking more than the recommended dose (overdose) can cause serious liver damage. In case of overdose, get medical help or contact a Poison Control Center (1-800-222-1222) right away. Prompt medical attention is critical even if you do not notice any signs or symptoms.

Directions

This product does not contain directions or complete warnings for adult use.

- Shake well before using
- Find the right dose on the chart on the chart below. If possible, use weight to determine dose; otherwise, use age.
- Only use the enclosed AccuSafe® syringe. Do not use any other syringe, dropper, spoon or dosing device when giving this medicine to your child.
- Remove cap, insert syringe to flow restrictor and invert bottle
- Pull back syringe until filled to the prescribed level and slowly dispense the liquid into your child’s mouth (towards the inner cheek)
- If needed, repeat dose every 4 hours while symptoms last
- Do not give more than 5 times in any 24-hour period (see overdose warning)
- Do not give more than 5 days unless directed by a doctor
- Replace cap tightly to maintain child resistance

mL = milliliter

Weight (lbs) | Age (yrs) | Dose (mL)
Under 24 | under 2 | Ask a doctor
24-35 | 2-3 | 5 mL

Other information

- Store at 20°-25°C (68°-77°F)
- AccuSafe® Oral dosing device enclosed
- Check expiration date on bottle or box before using.

Inactive ingredients

benzoic acid, carboxymethylcellulose, glycerin, natural grape flavor, microcrystalline cellulose, sucrose, sodium benzoate, water, xanthan gum

FOR DIAPER RASH
BOUDREAUX’S BUTT PASTE ® Diaper Rash Ointment

Drug Facts

Active ingredient Purpose

Zinc oxide, 16%...................................................Skin protectant

Uses

- Helps treat and prevent diaper rash

- Protects chafed skin due to diaper rash and helps seal out wetness

Warnings

For external use only

When using this product avoid contact with the eyes

Stop use and ask a doctor if condition worsens or does not improve after 7 days

Keep out of the reach of children to prevent accidental ingestion

If swallowed, seek medical help or call Poison Control Center (1-800-222-1222) immediately

Directions

- Change wet and soiled diaper immediately

- Cleanse the diaper area and allow to dry

- Apply ointment liberally and as often as necessary with each diaper change and especially when exposed to wet diapers for a prolonged period of time, such as bedtime

Other information

- Store at room temperature 20°- 27°C (68°- 80°F)
- Remove seal from jar before use

- Use with infants, children and adults

- Will stain clothing and fabric

Inactive ingredients castor oil, mineral oil, paraffin, peruvian balsam, white petrolatum

Questions?

1-855-785-2888 www.buttpaste.com

FOR TUMMYSTM

GAS RELIEF DROPS Simethicone / Antigas

Drug Facts

Active ingredient (in each 0.3 mL)

Simethicone Emulsion USP 66.7 mg/ Simethicone 20 mg

Purpose

Antigas

Uses

Relieves discomfort of infant gas frequently caused by excessive swallowing of air or certain formulas or food

Directions

■ shake well before using

■ only use enclosed syringe; fill to prescribed level and dispense liquid slowly into child’s mouth, toward inner cheek

■ all dosages may be repeated as needed, after meals and at bedtime or as directed by a physician. Do not exceed 12 doses per day.

■ dosage can also be mixed with 1 oz. of cool water, infant formula or other suitable liquids

■ for best results, clean syringe after each use and replace original cap

If possible, use weight to determine dose; otherwise use age.

mL = milliliters

Age (yrs) | Weight (lbs) | Dose
Newborns & Infants under 2 years | under 24 | 0.3 mL
Children 2 years and over | 24 and over | 0.6 mL

Other information

■ do not freeze ■ store at room temperature 20˚-25˚C (68˚-77˚F)

■ See bottle or box for lot number and expiration date

Inactive ingredients

carmellose sodium,citric acid, microcrystalline cellulose, natural strawberry flavor, propylene glycol, purified water, sodium benzoate, sucralose, xanthan gum

FOR TUMMYSTM

GRIPE WATER

Supplement Facts
Serving Size: 5 mL
Servings per Container: about 12
Amount per Serving | % Daily Value
Zingiber officinale (Ginger) Root Extract 5 mg | †
Foeniculum vulgare (Fennel) Seed Extract 4mg | †
†Daily Value not established

Other ingredients

purified water, agave, glycerin, natural ginger flavor, potassium sorbate, citric acid, xanthan gum

Suggested Use
Age | Dose
2 to 4 weeks | 2.5 mL
1 to 6 months | 5 mL
6 months and older | 10 mL
Adults | 30 mL

SHAKE WELL. May be taken directly using the dispenser included. May be given up to six times in a 24 hour period. If necessary to repeat dosage, wait a minimum of 30 minutes. Do not use if safety seal is broken or missing.

Keep out of reach of children.

In some infants, a rare allergic reaction may occur. Do not exceed recommended dosage.

Do not use if

▪ child has a history of kidney failure or renal problems ▪ child is allergic to any of the ingredients in this product Always consult your health care provider before giving this or any supplement to an infant. ▪ Store at room temperature.

FOR NOSESTM

SALINE SPRAY + DROPS

Uses

–Helps loosen mucus secretions to aid aspiration and removal from nose and sinuses, allowing for easier breathing. For infants this can be assisted with the use of our specially designed “Soft Tip” Nasal Aspirator.

Warnings

Keep out of reach of children.

▪ The use of this dispenser by more than one person may spread infection.

▪ Wipe nozzle clean after each use.

Directions

(For nasal use only)

▪ Infants: 2 to 6 drops in each nostril as often as needed or as directed by your doctor.

▪Children: 2 to 6 sprays or drops into each nostril as often as needed or as directed by a doctor.

Store at 20°-25°C (68°-77°F).

See bottle for lot and expiration date.

Ingredients:

water, sodium chloride, glycerin, sodium benzoate, benzoic acid

PRINCIPAL DISPLAY PANEL

Little Remedies®

New Baby Essentials Kit

INFANT FEVER/PAIN RELIEVER

ACETAMINOPHEN / FEVER/PAIN RELIEVER

2 FL OZ (59 mL)

Syringe Included

GAS DROPS

SIMETHICONE /ANTIGAS

1 FL OZ (30 mL)

Syringe Included

DIAPER RASH OINTMENT

ZINC OXIDE / SKIN PROTECTANT

2 OZ (57 g)

SALINE SPRAY + DROPS

0.5 FL OZ (15 mL)

GRIPE WATER

GINGER / FENNEL SUPPLEMENT

2 FL OZ (59 mL)

Syringe Included

Nasal Aspirator